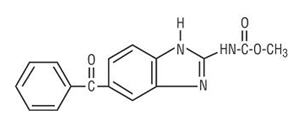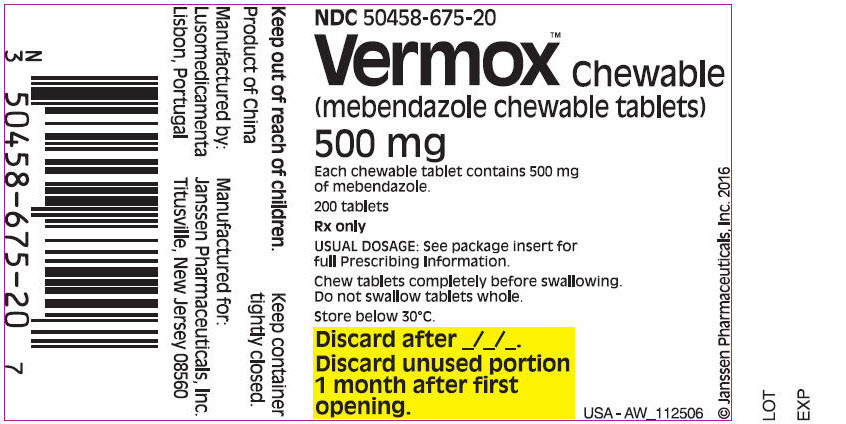 DRUG LABEL: VERMOX
NDC: 50458-675 | Form: TABLET, CHEWABLE
Manufacturer: Janssen Pharmaceuticals, Inc.
Category: prescription | Type: HUMAN PRESCRIPTION DRUG LABEL
Date: 20211005

ACTIVE INGREDIENTS: mebendazole 500 mg/1 1
INACTIVE INGREDIENTS: CROSPOVIDONE (120 .MU.M); magnesium stearate; microcrystalline cellulose; povidone, unspecified; water; strawberry; sucralose

HIGHLIGHTS OF PRESCRIBING INFORMATION

These highlights do not include all the information needed to use VERMOX™ CHEWABLE safely and effectively. See full prescribing information for VERMOX™ CHEWABLE.
VERMOX™ CHEWABLE (mebendazole chewable tablets), for oral use
Initial U.S. Approval: 1974

RECENT MAJOR CHANGES

Dosing and Administration (2) | 9/2021

1 INDICATIONS AND USAGE

VERMOX™ CHEWABLE is an anthelmintic indicated for the treatment of patients one year of age and older with gastrointestinal infections caused by:

- Ascaris lumbricoides (roundworm) and
- Trichuris trichiura (whipworm) (1).

2 DOSAGE AND ADMINISTRATION

- The recommended dosage in patients one year of age and older is one single tablet of VERMOX™ CHEWABLE 500 mg taken as a single dose, chewed completely before swallowing (2).
- See Full Prescribing Information for administration instructions for patients who have difficulty chewing the tablets (2)

3 DOSAGE FORMS AND STRENGTHS

Chewable Tablet: 500 mg (3)

4 CONTRAINDICATIONS

- Patients with a known hypersensitivity to the drug or its excipients (4)

5 WARNINGS AND PRECAUTIONS

- Risk of Convulsions: Convulsions in infants below the age of 1 year have been reported (5.1)
- Hematologic Effects: Neutropenia and agranulocytosis have been reported in patients receiving mebendazole at higher doses and for prolonged duration. Monitor blood counts in these patients (5.2)
- Metronidazole and Serious Skin Reactions: Stevens-Johnson syndrome/toxic epidermal necrolysis (SJS/TEN) have been reported with the concomitant use of mebendazole and metronidazole. Avoid concomitant use of mebendazole and metronidazole (5.3)

6 ADVERSE REACTIONS

Adverse reactions reported in clinical trials were anorexia, abdominal pain, diarrhea, flatulence, nausea, vomiting and rash. (6.1).

To report SUSPECTED ADVERSE REACTIONS, contact Janssen Pharmaceuticals, Inc. at 1-800-JANSSEN (1-800-526-7736) or FDA at 1-800-FDA-1088 or www.fda.gov/medwatch.

FULL PRESCRIBING INFORMATION

1 INDICATIONS AND USAGE

VERMOX™ CHEWABLE is indicated for the treatment of patients one year of age and older with gastrointestinal infections caused by Ascaris lumbricoides (roundworm) and Trichuris trichiura (whipworm).

2 DOSAGE AND ADMINISTRATION

The recommended dosage in patients one year of age and older is one VERMOX™ CHEWABLE 500 mg tablet taken as a single dose.

Chew VERMOX™ CHEWABLE 500 mg tablet completely before swallowing. Do not swallow the tablet whole.

For patients who have difficulty chewing the tablet, approximately 2 mL to 3 mL of drinking water can be added to a suitably sized spoon and the VERMOX™ CHEWABLE 500 mg tablet placed into the water. Within 2 minutes, the tablet absorbs the water and turns into a soft mass with semi-solid consistency, which can then be swallowed.

VERMOX™ CHEWABLE 500 mg tablet can be taken without regard to food intake [see Clinical Pharmacology (12.3)].

3 DOSAGE FORMS AND STRENGTHS

Chewable Tablet: 500 mg round, flat radius-edged white to yellowish chewable tablet that is debossed with "M/500" on one side and "J" on the other side.

4 CONTRAINDICATIONS

VERMOX™ CHEWABLE is contraindicated in persons with a known hypersensitivity to the drug or its excipients.

5 WARNINGS AND PRECAUTIONS

5.1 Risk of Convulsions

Convulsions have been reported in infants below the age of 1 year during post-marketing experience with mebendazole [see Adverse Reactions (6.2)].

5.2 Hematologic Effects

Agranulocytosis and neutropenia have been reported with mebendazole use at higher doses and for more prolonged durations than is recommended for the treatment of soil-transmitted helminth infections. Monitor blood counts if VERMOX™ CHEWABLE is used at higher doses or for prolonged duration.

5.3 Metronidazole Drug Interaction and Serious Skin Reactions

Stevens-Johnson syndrome/toxic epidermal necrolysis (SJS/TEN) have been reported with the concomitant use of mebendazole and metronidazole. Avoid concomitant use of mebendazole and metronidazole.

6 ADVERSE REACTIONS

6.1 Clinical Studies

Because clinical trials are conducted under widely varying conditions, adverse reaction rates observed in the clinical trials of a drug cannot be directly compared to rates in the clinical trials of another drug and may not reflect the rates observed in practice.

The safety of mebendazole was evaluated in 6276 adult and pediatric subjects one year of age and older who participated in 39 clinical trials for treatment of single or mixed parasitic infections of the gastrointestinal tract. In these trials, the formulations, dosages and duration of mebendazole treatment varied. Adverse reactions reported in mebendazole-treated subjects from the 39 clinical trials are shown in Table 1 below.

Table 1: Adverse Reactions Reported in Mebendazole-Treated Subjects from 39 Clinical Trials [Includes mebendazole formulations, dosages and treatment duration other than VERMOX™ CHEWABLE 500 mg tablet]

Adverse Reaction(s)

Gastrointestinal Disorders

Anorexia

Abdominal Pain

Diarrhea

Flatulence

Nausea

Vomiting

Skin and Subcutaneous Tissue Disorders

Rash

Clinical Studies with Mebendazole Chewable 500 mg Tablet

The safety profile of mebendazole chewable 500 mg tablets administered as a single dose was evaluated in 677 pediatric subjects aged 1 to 16 years and in 34 adults. The safety profile was consistent with the known safety profile of mebendazole.

6.2 Postmarketing Experience

The following adverse reactions have been identified in adult and pediatric patients postmarketing with mebendazole formulations and dosages other than the VERMOX™ CHEWABLE 500 mg tablet. Because these reactions are reported voluntarily from a population of uncertain size, it is not always possible to reliably estimate their frequency or establish a causal relationship to drug exposure.

Table 2: Adverse Reactions Identified During Postmarketing Experience with Mebendazole [Includes mebendazole formulations, dosages and treatment durations other than VERMOX™ CHEWABLE 500 mg tablet]
 | Adverse Reaction(s)
Blood and Lymphatic System Disorders | Agranulocytosis, Neutropenia
Immune System Disorders | Hypersensitivity including anaphylactic reactions
Nervous System Disorders | Convulsions, Dizziness
Hepatobiliary Disorders | Hepatitis, Abnormal liver tests
Renal and Urinary Disorders | Glomerulonephritis
Skin and Subcutaneous Tissue Disorders | Toxic epidermal necrolysis, Stevens-Johnson syndrome, Exanthema, Angioedema, Urticaria, Alopecia

7 DRUG INTERACTIONS

Concomitant use of mebendazole and metronidazole should be avoided [see Warnings and Precautions (5.3)].

8 USE IN SPECIFIC POPULATIONS

8.1 Pregnancy

Risk Summary

The available published literature on mebendazole use in pregnant women has not reported a clear association between mebendazole and a potential risk of major birth defects or miscarriages [see Data]. There are risks to the mother and fetus associated with untreated helminthic infection during pregnancy [see Clinical Considerations].

In animal reproduction studies, adverse developmental effects (i.e., skeletal malformations, soft tissue malformations, decreased pup weight, embryolethality) were observed when mebendazole was administered to pregnant rats during the period of organogenesis at single oral doses as low as 10 mg/kg (approximately 0.2-fold the maximum recommended human dose (MRHD)). Maternal toxicity was present at the highest of these doses [see Data].

The estimated background risk of major birth defects and miscarriage for the indicated populations is unknown. All pregnancies have a background risk of birth defect, loss, or other adverse outcomes. In the U.S. general population, the estimated background risk of major birth defects and miscarriage in clinically recognized pregnancies is 2–4% and 15–20%, respectively.

Clinical Considerations

Disease-Associated Maternal and/or Embryo/Fetal Risks

Untreated soil-transmitted helminth infections in pregnancy are associated with adverse outcomes including maternal iron deficiency anemia, low birth weight, neonatal and maternal death.

Data

Human Data

Several published studies, including prospective pregnancy registries, case-control, retrospective cohort, and randomized controlled studies, have reported no association between mebendazole use and a potential risk of major birth defects or miscarriage. Overall, these studies did not identify a specific pattern or frequency of major birth defects with mebendazole use. However, these studies cannot definitely establish the absence of any mebendazole-associated risk because of methodological limitations, including recall bias, confounding factors and, in some cases, small sample size or exclusion of first trimester mebendazole exposures.

TERATOGENIC EFFECTS

Animal Data

Embryo-fetal developmental toxicity studies in rats revealed no adverse effects on dams or their progeny at doses up to 2.5 mg/kg/day on gestation days 6–15 (the period of organogenesis). Dosing at ≥10 mg/kg/day resulted in a lowered body weight gain and a decreased pregnancy rate. Maternal toxicity, including body weight loss in one animal and maternal death in 11 of 20 animals, was seen at 40 mg/kg/day. At 10 mg/kg/day, increased embryo-fetal resorption (100% were resorbed at 40 mg/kg/day), decreased pup weight and increased incidence of malformations (primarily skeletal) were observed. Mebendazole was also embryotoxic and teratogenic in pregnant rats at single oral doses during organogenesis as low as 10 mg/kg (approximately 0.2-fold the MRHD, based on mg/m^2).

In embryo-fetal developmental toxicity studies in mice dosed on gestation days 6–15, doses of 10 mg/kg/day and higher resulted in decreased body weight gain at 10 and 40 mg/kg/day and a higher mortality rate at 40 mg/kg/day. At doses of 10 mg/kg/day (approximately 0.1-fold the MRHD, based on mg/m^2) and higher, embryo-fetal resorption increased (100% at 40 mg/kg) and fetal malformations, including skeletal, cranial, and soft tissue anomalies, were present. Dosing of hamsters and rabbits did not result in embryotoxicity or teratogenicity at doses up to 40 mg/kg/day (0.6 to 1.6-fold the MRHD, based on mg/m^2).

In a peri- and post-natal toxicity study in rats, mebendazole did not adversely affect dams or their progeny at 20 mg/kg/day. At 40 mg/kg (0.8-fold the MRHD, based on mg/m^2), a reduction of the number of live pups was observed and there was no survival at weaning. No abnormalities were found on gross and radiographic examination of pups at birth.

8.2 Lactation

Risk Summary

Limited data from case reports demonstrate that a small amount of mebendazole is present in human milk following oral administration. There are no reports of effects on the breastfed infant, and the limited reports on the effects on milk production are inconsistent. The limited clinical data during lactation precludes a clear determination of the risk of VERMOX™ CHEWABLE to a breastfed infant; therefore, developmental and health benefits of breastfeeding should be considered along with the mother's clinical need for VERMOX™ CHEWABLE and any potential adverse effects on the breastfed infant from VERMOX™ CHEWABLE or from the underlying maternal condition.

8.4 Pediatric Use

The safety and effectiveness of VERMOX™ CHEWABLE 500 mg tablets have been established in pediatric patients 1 to 16 years of age. Use of VERMOX™ CHEWABLE 500 mg tablets in children is supported by evidence from adequate and well-controlled studies of VERMOX™ CHEWABLE 500 mg tablets [see Clinical Studies (14)].

The safety and effectiveness of mebendazole, including VERMOX™ CHEWABLE have not been established in pediatric patients less than one year of age. Convulsions have been reported with mebendazole use in this age group [see Warnings and Precautions (5.1) and Adverse Reactions (6.2)].

8.5 Geriatric Use

Clinical studies of mebendazole did not include sufficient numbers of subjects aged 65 and older to determine whether they respond differently from younger subjects.

8.6 Adult Use

The safety and effectiveness of VERMOX™ CHEWABLE 500 mg tablets have been established in adults for the treatment of gastrointestinal infections by T. trichiura and A. lumbricoides. Use of VERMOX™ CHEWABLE 500 mg tablets in adults for these indications is supported by evidence from an adequate and well-controlled trial in pediatric patients ages 1 to 16 years [see Clinical Studies (14.1)], safety data in adults [see Adverse Reactions (6.1)], pharmacokinetic data in adults [see Clinical Pharmacology (12.3)], and the evidence from published literature.

10 OVERDOSAGE

In patients treated at dosages substantially higher than recommended or for prolonged periods of time, the following adverse reactions have been reported: alopecia, reversible transaminase elevations, hepatitis, agranulocytosis, neutropenia, and glomerulonephritis.

Symptoms and signs

In the event of accidental overdose, gastrointestinal signs/symptoms may occur.

Treatment

There is no specific antidote.

11 DESCRIPTION

VERMOX™ CHEWABLE (mebendazole chewable tablets) is an orally administered anthelmintic. Chemically, it is methyl 5-benzoylbenzimidazole-2-carbamate. Its molecular formula is C16H13N3O3. Its molecular weight is 295.30. It has the following chemical structure:

Mebendazole exhibits polymorphism. The polymorph used in VERMOX™ CHEWABLE is polymorph form C. Mebendazole is a white to almost white powder. It is practically insoluble in water, in ethanol (96%) and in methylene chloride.

Each round, flat radius-edged white to yellowish chewable tablet contains 500 mg of mebendazole and is debossed with "M/500" on one side and "J" on the other side.

Inactive ingredients consist of: crospovidone, magnesium stearate, microcrystalline cellulose, povidone, purified water, strawberry flavor and sucralose.

12 CLINICAL PHARMACOLOGY

12.1 Mechanism of Action

Mebendazole, a benzimidazole, is an anthelmintic [see Microbiology (12.4)].

12.3 Pharmacokinetics

Absorption

Following oral administration of VERMOX™ CHEWABLE 500 mg tablet, the majority of the dose remains in the gastrointestinal tract where it exerts an anthelmintic effect locally. Dosing the VERMOX™ CHEWABLE 500 mg tablet with a high fat meal increases the bioavailability of mebendazole. In the clinical studies conducted in pediatric patients with soil transmitted helminth infections, the majority of these patients were administered VERMOX™ CHEWABLE 500 mg tablets with food.

Mean plasma pharmacokinetic parameters of mebendazole in healthy adult subjects under fasted and fed conditions are summarized in Table 3.

Table 3: Mean (SD) Plasma Pharmacokinetic Parameters After a Single VERMOX™ CHEWABLE 500 mg Dose in Healthy Adult Subjects (n=16) Under Fasted and Fed (High-fat Meal) Conditions
Parameter | Fasted | Fed
Cmax (ng/mL) | 14.0 (9.17) | 56.2 (35.8)
Tmax (h) [median (range)] | 1.5 (0.5–3.0) | 4.0 (2.0–6.0)
AUClast (ng.h/mL) | 175 (129) | 456 (249)

Distribution

The plasma protein binding of mebendazole is 90 to 95%. The volume of distribution is 1 to 2 L/kg, indicating that absorbed mebendazole penetrates areas outside the vascular space.

Metabolism

Orally administered mebendazole is extensively metabolized primarily by the liver. Plasma concentrations of its major metabolites (hydrolyzed and reduced forms of mebendazole) are higher than those of mebendazole. Impaired hepatic function, impaired metabolism, or impaired biliary elimination may lead to higher plasma levels of mebendazole.

Elimination

Mebendazole, the conjugated forms of mebendazole, and its metabolites likely undergo some degree of enterohepatic recirculation. The apparent elimination half-life after an oral dose ranges from 3 to 6 hours in most patients. Less than 2% of orally administered mebendazole is excreted in urine and the remainder in the feces as unchanged drug or its metabolites.

Specific Populations

Pediatric

Based on a limited number of blood samples, the pharmacokinetic results following single-dose administration of a 500 mg mebendazole chewable tablet to pediatric patients (age 1 to 16 years) with single or mixed infections of T. trichiura and/or A. lumbricoides indicated that children aged 1 to 3 years have higher systemic exposure than adults.

12.4 Microbiology

Mechanism of Action

Mebendazole interferes with cellular tubulin formation in the helminth and causes ultrastructural degenerative changes in its intestine. As a result, its glucose uptake and the digestive and reproductive functions are disrupted, leading to immobilization, inhibition of egg production and death of the helminth.

Antimicrobial Activity

Mebendazole is active against:

Ascaris lumbricoides

Trichuris trichiura

Resistance

There is a potential for development of resistance to mebendazole. The mechanism of resistance to mebendazole is likely due to changes of beta-tubulin protein, which reduces binding of mebendazole to beta-tubulin; however, the clinical significance of this is not known.

13 NONCLINICAL TOXICOLOGY

13.1 Carcinogenesis, Mutagenesis, Impairment of Fertility

In carcinogenicity tests of mebendazole in mice and rats, no carcinogenic effects were seen at doses as high as 40 mg/kg (0.4 to 0.8-fold the MRHD, based on mg/m^2) given daily over two years. No mutagenic activity was observed with mebendazole in a bacterial reverse gene mutation test. Mebendazole was mutagenic in the absence of S-9 when tested using a continuous (24 hour) treatment incubation period in the mouse lymphoma thymidine kinase assay. Mebendazole was aneugenic in vitro in mammalian somatic cells. In the in vivo mouse micronucleus assay, orally administered mebendazole induced an increased frequency of micronucleated polychromatic erythrocytes with evidence suggestive of aneugenicity. Doses up to 40 mg/kg in rats (0.8-fold the MRHD, based on mg/m^2), given to males for 60 days and to females for 14 days prior to gestation, had no effect upon fetuses and offspring.

14 CLINICAL STUDIES

The efficacy of VERMOX™ CHEWABLE 500 mg tablets was evaluated in a double-blind, randomized, placebo controlled trial conducted in Africa in 295 pediatric patients between the ages of 1 year to 16 years of age with A. lumbricoides and/or T. trichiura infections. Patients were stratified by worm type and randomized to receive either VERMOX™ CHEWABLE 500 mg tablet (N=149) or placebo (N=146) at the baseline visit (double-blind period). After the 19 day double-blind period, all subjects received a single VERMOX™ CHEWABLE 500 mg tablet (open-label period).

Clinical cure was defined as zero egg count (A. lumbricoides and/or T. trichiura) at the end of the double-blind period (Day 19) in patients with positive egg count for the respective worm(s) at baseline. Patients with missing stool sample at Day 19 were considered not cured (Table 4).

Table 4: Clinical Response at the End of the Double-Blind Period (Day 19) for A. lumbricoides and T. trichiura
Infection Type | VERMOX™ CHEWABLE 500 mg All Patients=149 [Some patients had mixed infection.] | Placebo All Patients=146 | Difference [Difference in cure rates, expressed in percentages, and based on Mantel Haenszel methods to account for stratification by site.] (95% CI)
A. lumbricoides | N=86 n (%) | N=81 n (%)
Cure | 72 (83.7) | 9 (11.1) | 72.6 (62.3, 82.7) [P-value <0.001 based on the Cochran-Mantel-Haenszel test, controlling for the effect of site.]
Failure [Failures include patients who tested positive for the worm at Visit 3 (Day 19, i.e. test-of-cure).] | 9 (10.5) | 67 (82.7)
Missing [Patients with missing stool sample at Day 19.] | 5 (5.8) | 5 (6.2)
T. trichiura | N=124 n (%) | N=119 n (%)
Cure | 42 (33.9) | 9 (7.6) | 26.2 (16.7, 35.6)
Failure | 76 (61.3) | 103 (86.6)
Missing | 6 (4.8) | 7 (5.8)

In patients treated with VERMOX™ CHEWABLE 500 mg, egg count reduction rate at the end of the double-blind period (Day 19) in patients with A. lumbricoides and/or T. trichiura was statistically significant (p<0.001) compared to placebo, 100% compared to 30.0% for A. lumbricoides, respectively, and 81.2% compared to 27.4% for T. trichiura, respectively.

16 HOW SUPPLIED/STORAGE AND HANDLING

VERMOX™ CHEWABLE tablets are supplied as 500 mg, round, flat radius-edged white to yellowish chewable tablets that are debossed with "M/500" on one side and "J" on the other side. They are supplied as follows:

Bottles of 200 tablets | NDC 50458-675-20

STORAGE AND HANDLING

Store below 30°C. Keep container tightly closed. Unused tablets should be discarded 1 month after the bottle is first opened. When the bottle is first opened this Discard After date should be written on the bottle label in the place provided.

17 PATIENT COUNSELING INFORMATION

Advise patients that:

- VERMOX™ CHEWABLE tablet must be chewed completely before swallowing. For patients who have difficulty chewing the tablet, VERMOX™ CHEWABLE tablet can be turned into a soft mass with semi-solid consistency by adding 2 mL to 3 mL of drinking water to a spoon then placing the tablet into the water, which can then be swallowed. [see Dosage and Administration (2)]
- VERMOX™ CHEWABLE tablet must not be swallowed whole. [see Dosage and Administration (2)]
- VERMOX™ CHEWABLE tablet can be taken with or without food. [see Dosage and Administration (2)]
- Taking VERMOX™ CHEWABLE tablet and metronidazole together may cause serious skin reactions and should be avoided. [see Warnings and Precautions (5.3)]

Product of China

Manufactured by:
Lusomedicamenta
Lisbon, Portugal

Manufactured for:
Janssen Pharmaceuticals, Inc.
Titusville, New Jersey 08560

© Janssen Pharmaceuticals, Inc. 2016

PRINCIPAL DISPLAY PANEL - 500 mg Tablet Bottle Label

NDC 50458-675-20

Vermox™ Chewable
(mebendazole chewable tablets)

500 mg

Each chewable tablet contains 500 mg
of mebendazole.

200 tablets

Rx only

USUAL DOSAGE: See package insert for
full Prescribing Information.

Chew tablets completely before swallowing.
Do not swallow tablets whole.

Store below 30°C.

Discard after _/_/_.
Discard unused portion
1 month after first
opening.

USA-AW_112506

© Janssen Pharmaceuticals, Inc. 2016